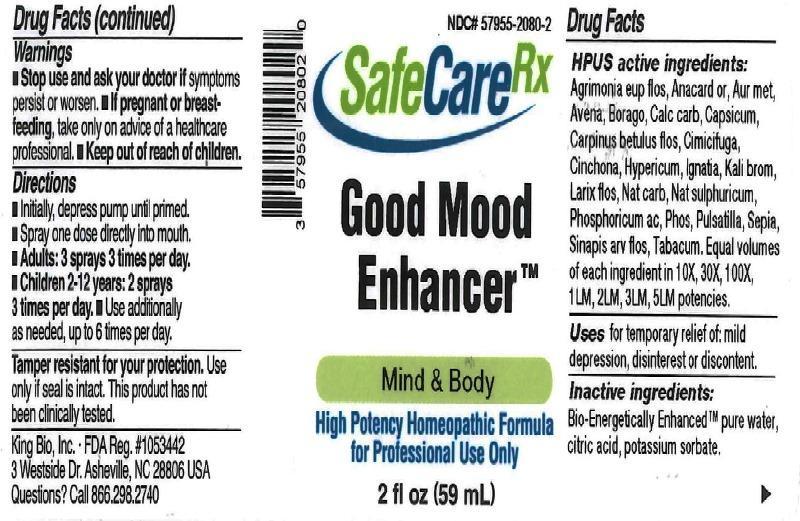 DRUG LABEL: Good Mood Enhancer
NDC: 57955-2080 | Form: LIQUID
Manufacturer: King Bio Inc.
Category: homeopathic | Type: HUMAN OTC DRUG LABEL
Date: 20161028

ACTIVE INGREDIENTS: AGRIMONIA EUPATORIA FLOWER 10 [hp_X]/10 mL; SEMECARPUS ANACARDIUM JUICE 10 [hp_X]/10 mL; GOLD 10 [hp_X]/10 mL; AVENA SATIVA FLOWERING TOP 10 [hp_X]/10 mL; BORAGE 10 [hp_X]/10 mL; OYSTER SHELL CALCIUM CARBONATE, CRUDE 10 [hp_X]/10 mL; CAPSICUM 10 [hp_X]/10 mL; CARPINUS BETULUS FLOWERING TOP 10 [hp_X]/10 mL; BLACK COHOSH 10 [hp_X]/10 mL; CINCHONA OFFICINALIS BARK 10 [hp_X]/10 mL; HYPERICUM PERFORATUM 10 [hp_X]/10 mL; STRYCHNOS IGNATII SEED 10 [hp_X]/10 mL; POTASSIUM BROMIDE 10 [hp_X]/10 mL; LARIX DECIDUA FLOWERING TOP 10 [hp_X]/10 mL; SODIUM CARBONATE 10 [hp_X]/10 mL; SODIUM SULFATE 10 [hp_X]/10 mL; PHOSPHORIC ACID 10 [hp_X]/10 mL; PHOSPHORUS 10 [hp_X]/10 mL; PULSATILLA VULGARIS 10 [hp_X]/10 mL; SEPIA OFFICINALIS JUICE 10 [hp_X]/10 mL; SINAPIS ARVENSIS FLOWERING/FRUITING TOP 10 [hp_X]/10 mL; TOBACCO LEAF 10 [hp_X]/10 mL
INACTIVE INGREDIENTS: ANHYDROUS CITRIC ACID; POTASSIUM SORBATE; WATER

Good Mood Enhancer™

ACTIVE INGREDIENT

Drug Facts__________________________________________________________________________________________________________

HPUS active ingredients: Agrimonia eupatoria, flos, Anacardium orientale, Aurum metallicum, Avena sativa, Borago officinalis, Calcarea carbonica, Capsicum annuum, Carpinus betulus, flos, Cimicifuga racemosa, Cinchona officinalis, Hypericum perforatum, Ignatia amara, Kali bromatum, Larix decidua, flos, Natrum carbonicum, Natrum sulphuricum, Phosphoricum acidum, Phosphorus, Pulsatilla, Sepia, Sinapis arvensis, flos, Tabacum. Equal volumes of each ingredient in 10X, 30X, 100X, 1LM, 2LM, 3LM, 5LM potencies.

INDICATIONS AND USAGE

Uses for temporary relief of: mild depression, disinterest or discontent.

Inactive Ingredients:

Bio-Energetically Enhanced™ pure water, citric acid and potassium sorbate.

Warnings

- Stop use and ask your doctor if symptoms persist or worsen.
- If pregnant or breast-feeding, take only on advice of a healthcare professional.

- Keep out of reach of children.

Directions

- Initially, depress pump until primed.
- Spray one dose directly into mouth.
- Adults 12 and up: 3 sprays 3 times per day.
- Children 2-12: 2 sprays 3 times per day.
- Children 2 mo-2 yr: 1 spray 3 times per day.

OTHER SAFETY INFORMATION

Tamper resistant for your protection. Use only if safety seal is intact. This product has not been clinically tested.

PURPOSE

Uses for temporary relief of:

- mild depression
- disinterest
- discontent